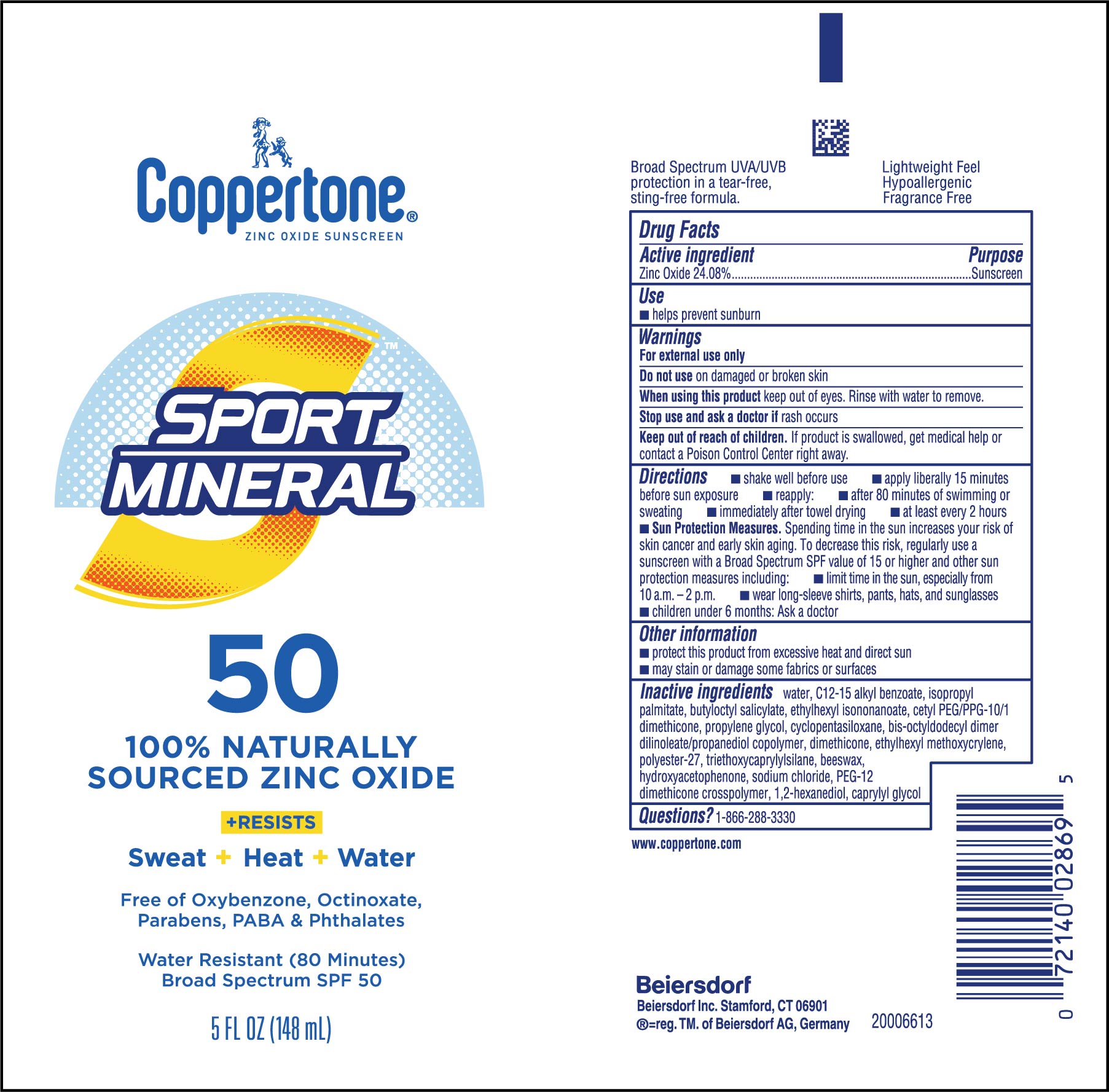 DRUG LABEL: Coppertone Sport Mineral Sunscreen SPF 50
NDC: 66800-0002 | Form: LOTION
Manufacturer: Beiersdorf Inc
Category: otc | Type: HUMAN OTC DRUG LABEL
Date: 20251231

ACTIVE INGREDIENTS: ZINC OXIDE 240.8 mg/1 mL
INACTIVE INGREDIENTS: POLYESTER-7; ISOPROPYL PALMITATE; ETHYLHEXYL METHOXYCRYLENE; BUTYLOCTYL SALICYLATE; WATER; ETHYLHEXYL ISONONANOATE; CETYL PEG/PPG-10/1 DIMETHICONE (HLB 2); CAPRYLYL GLYCOL; TRIETHOXYCAPRYLYLSILANE; SYNTHETIC BEESWAX; CYCLOMETHICONE 5; HYDROXYACETOPHENONE; SODIUM CHLORIDE; PEG-12 DIMETHICONE; 1,2-HEXANEDIOL; PROPYLENE GLYCOL; ALKYL (C12-15) BENZOATE; BIS-OCTYLDODECYL DIMER DILINOLEATE/PROPANEDIOL COPOLYMER; DIMETHICONE

Sport Mineral Lotion SPF 50

Drug Facts

Active Ingredient

Zinc Oxide 24.08%

Purpose

sunscreen

Use

helps prevent sunburn

Warnings

For external use only

Do not useon damaged or broken skin

When using this product keep out of eyes. Rinse with water to remove.

Stop use and ask a doctor if rash occurs

Keep out of reach of children. If product is swallowed, get medical help or contac a Poison Control Center right away.

WHEN USING

When using this productkeep out of eyes. Rinse with water to remove.

Stop use and ask a doctor ifrash occurs

Keep out of reach of children.If product is swallowed, get medical help or contact a Poison Control Center right away.

Directions

- shake well before use
- apply liberally 15 minutes before sun exposure
- reapply:
  - after 80 minutes of swimming or sweating
  - immediately after towel drying
  - at least every 2 hours
  - Sun Protection Measures. Spending time in the sun increases your risk of skin cancer and early skin aging. To decrease this risk, regularly use a sunscreen with a Broad Spectrum SPF value of 15 or higher and other sun protection measures including:
  - limit time in the sun, expecially from 10 a.m. - 2 p.m.
  - wear long-sleeve shirts, pants, hats and sunglasses
  - children under 6 months: Ask a doctor

Other Information

- protect this product from excessive heat and direct sun
- may stain or damage some fabrics or surfaces

Inactive Ingredients

water, C12-15 alkyl benzoate, isopropyl palmitate, butyloctyl salicylate, ethylhexyl isononanoate, cetyl PED-PPG-10/1 dimethicone, propylene glycol, cyclopentasilxane, bis-octyldodecyl dimer dilinoleate/propanediol copolymer, dimethicone, ethylhexyl methoxycrylene, polyester-27, triethoxycaprylylsilane, beeswax, hydroxyacetophenone, sodium chloride, PEG-12 dimethicone crosspolymer, 1,2-hexanediol, caprylyl glycol

Questions

1-866-288-3330

PACKAGE LABEL

Coppertone®

SUNSCREEN LOTION

SPORT MINERAL

SPF 50

100% naturally sourced zinc-oxide

Free of oxybenzone, oxtinoxate, PABA, parabens, phthalate

Water Resistant (80 minutes)

Broad Spectrum SPF 50

5 FL OZ (148 mL)